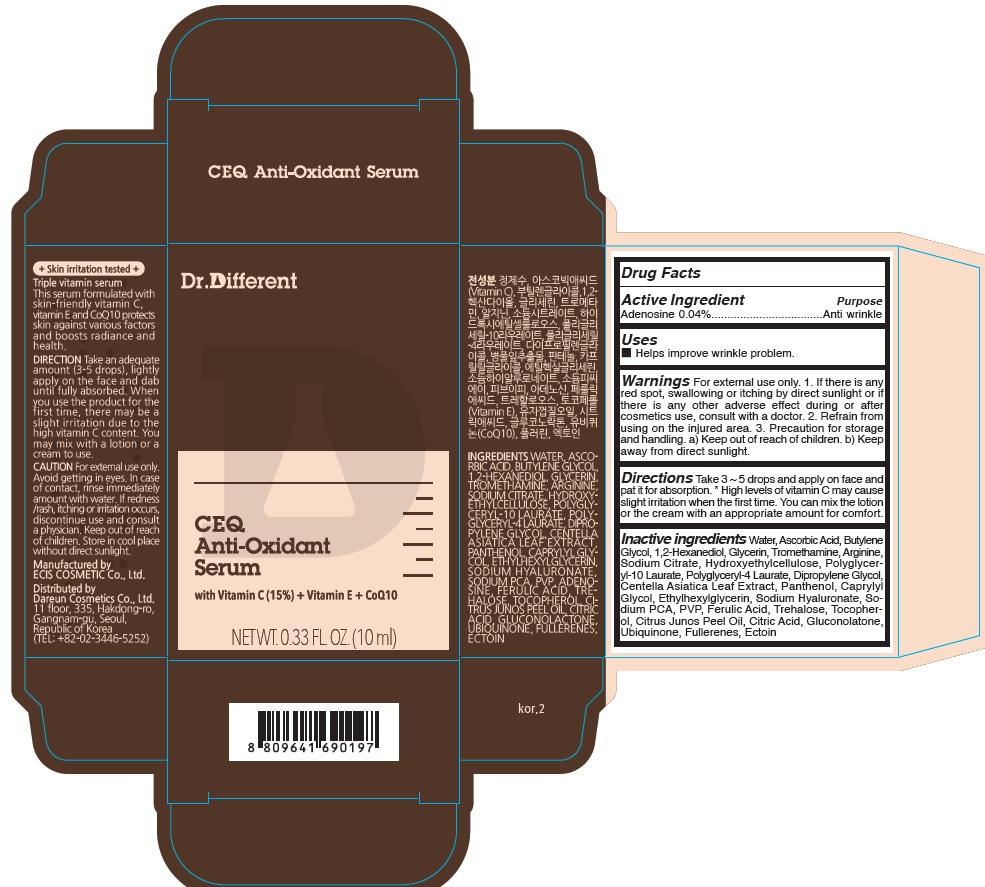 DRUG LABEL: Dr.Different CEQ Anti Oxidant Serum
NDC: 81710-080 | Form: LIQUID
Manufacturer: Dareun Cosmetics Co., Ltd.
Category: otc | Type: HUMAN OTC DRUG LABEL
Date: 20210413

ACTIVE INGREDIENTS: Adenosine 0.04 g/100 mL
INACTIVE INGREDIENTS: WATER; Ascorbic Acid; BUTYLENE GLYCOL

ACTIVE INGREDIENT

Adenosine 0.04%

INACTIVE INGREDIENTS

Water, Ascorbic Acid, Butylene Glycol, 1,2-Hexanediol, Glycerin, Tromethamine, Arginine, Sodium Citrate, Hydroxyethylcellulose, Polyglyceryl-10 Laurate, Polyglyceryl-4 Laurate, Dipropylene Glycol, Centella Asiatica Leaf Extract, Panthenol, Caprylyl Glycol, Ethylhexylglycerin, Sodium Hyaluronate, Sodium PCA, PVP, Ferulic Acid, Trehalose, Tocopherol, Citrus Junos Peel Oil, Citric Acid, Gluconolactone, Ubiquinone, Fullerenes, Ectoin

PURPOSE

Anti wrinkle

WARNINGS

For external use only.
1. If there is any red spot, swallowing or itching by direct sunlight or if there is any other adverse effect during or after cosmetics use, consult with a doctor.
2. Refrain from using on the injured area.
3. Precaution for storage and handling.
a) Keep out of reach of children.
b) Keep away from direct sunlight.

KEEP OUT OF REACH OF CHILDREN

Uses

■ Helps improve wrinkle problem.

Directions

Take 3 ~ 5 drops and apply on face and pat it for absorption.
* High levels of vitamin C may cause slight irritation when the first time. You can mix the lotion or the cream with an appropriate amount for comfort.